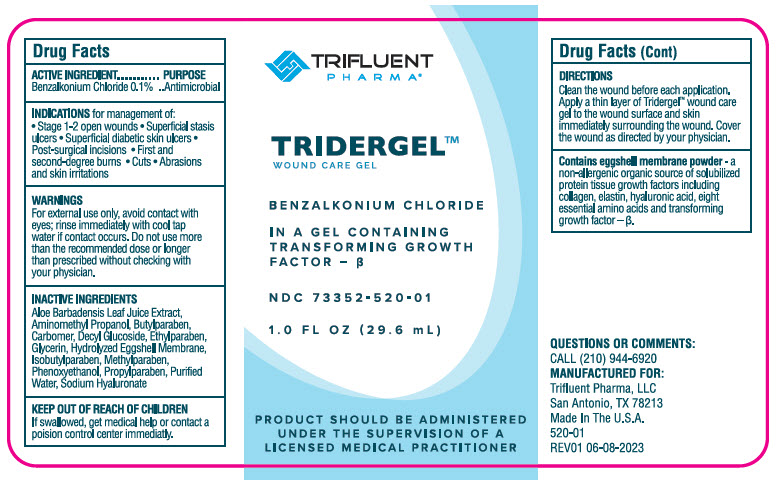 DRUG LABEL: Tridergel
NDC: 73352-520 | Form: GEL
Manufacturer: Trifluent Pharma LLC
Category: otc | Type: HUMAN OTC DRUG LABEL
Date: 20251013

ACTIVE INGREDIENTS: BENZALKONIUM CHLORIDE 0.001 g/1 mL
INACTIVE INGREDIENTS: WATER; EGG SHELL MEMBRANE; CARBOMER HOMOPOLYMER, UNSPECIFIED TYPE; GLYCERIN; AMINOMETHYLPROPANOL; HYALURONATE SODIUM; ALOE VERA LEAF; PHENOXYETHANOL; METHYLPARABEN; ETHYLPARABEN; ISOBUTYLPARABEN; BUTYLPARABEN; PROPYLPARABEN

TRIDERGEL™

Drug Facts

Active Ingredients

Benzalkonium Chloride (0.1%)

Purpose

Antimicrobial

Indications for management of:

- Stage 1-2 open wounds
- Superficial stasis ulcers
- Superficial diabetic skin ulcers
- Post-surgical incisions
- First and second-degree burns
- Cuts
- Abrasions and skin irritations

Warnings

For external use only.

When using this product avoid contact with eyes; rinse immediately with cool tap water if contact occurs.

Do not use more than the recommended dose or longer than prescribed without checking with your physician. Talk with your physician before you use any other medicines or cleansers on your skin. Ask your physician before prolonged sun exposure. If your symptoms do not improve or they worsen, contact your physician

Keep out of reach of children. If swallowed, get medical help or contact a Poison Control Center (1-800-222-1222) immediately.

Directions

- Clean the wound before each application
- Apply a thin layer of Tridergel™ wound care gel to the wound surface and skin immediately surrounding the wound
- Cover the wound as directed by your physician

Inactive Ingredients

Aloe Barbadensis Leaf Juice Extract, Aminomethyl Propanol, Butylparaben, Carbomer, Decyl Glucoside, Ethylparaben, Glycerin, Hydrolyzed Eggshell Membrane, Isobutylparaben, Methylparaben, Phenoxyethanol, Propylparaben, Purified Water, Sodium Hyaluronate.

QUESTIONS OR COMMENTS

CALL (210) 944-6920

PRINCIPAL DISPLAY PANEL - 29.6 mL Bottle Label

TRIFLUENT
PHARMA®

TRIDERGEL™
WOUND CARE GEL

BENZALKONIUM CHLORIDE

IN A GEL CONTAINING
TRANSFORMING GROWTH
FACTOR – β

NDC 73352-520-01

1.0 FL OZ (29.6 mL)

PRODUCT SHOULD BE ADMINISTERED
UNDER THE SUPERVISION OF A
LICENSED MEDICAL PRACTITIONER